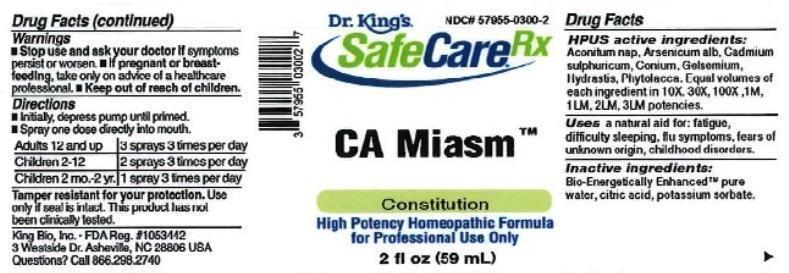 DRUG LABEL: CA Miasm
NDC: 57955-0300 | Form: LIQUID
Manufacturer: King Bio Inc.
Category: homeopathic | Type: HUMAN OTC DRUG LABEL
Date: 20161215

ACTIVE INGREDIENTS: ACONITUM NAPELLUS 10 [hp_X]/59 mL; ARSENIC TRIOXIDE 10 [hp_X]/59 mL; CADMIUM SULFATE 10 [hp_X]/59 mL; CONIUM MACULATUM FLOWERING TOP 10 [hp_X]/59 mL; GELSEMIUM SEMPERVIRENS ROOT 10 [hp_X]/59 mL; GOLDENSEAL 10 [hp_X]/59 mL; PHYTOLACCA AMERICANA ROOT 10 [hp_X]/59 mL
INACTIVE INGREDIENTS: WATER; ANHYDROUS CITRIC ACID; POTASSIUM SORBATE

CA Miasm™

ACTIVE INGREDIENT

Drug Facts__________________________________________________________________________________________________________

HPUS active ingredients: Aconitum napellus, Arsenicum album, Cadmium sulphuricum, Conium maculatum, Gelsemium sempervirens, Hydrastis canadensis, Phytolacca decandra. Equal volumes of each ingredient in 10X, 30X, 100X, 1M, 1LM, 2LM, 3LM potencies.

INDICATIONS AND USAGE

Uses a natural aid for: fatigue, difficulty sleeping, flu symptoms, fears of unknown origin, childhood disorders.

INACTIVE INGREDIENT

Inactive Ingredients: Bio-Energetically Enhanced™ pure water, citric acid and potassium sorbate.

Warnings

- Stop use and ask your doctor if symptoms persist or worsen.
- If pregnant or breast-feeding, take only on advice of a healthcare professional.

- Keep out of reach of children.

Directions

- Initially, depress pump until primed.
- Spray one dose directly into mouth.
- Adults: 3 sprays 3 times per day.
- Children (2-12 years): 2 sprays 3 times per day.
- Children (1 month-2 years): 1 spray 3 times per day.

OTHER SAFETY INFORMATION

Tamper resistant for your protection. Use only if safety seal is intact. This product has not been clinically tested.

PURPOSE

Uses a natural aid for:

- fatigue
- difficulty sleeping
- flu symptoms
- fears of unknown origin
- childhood disorders